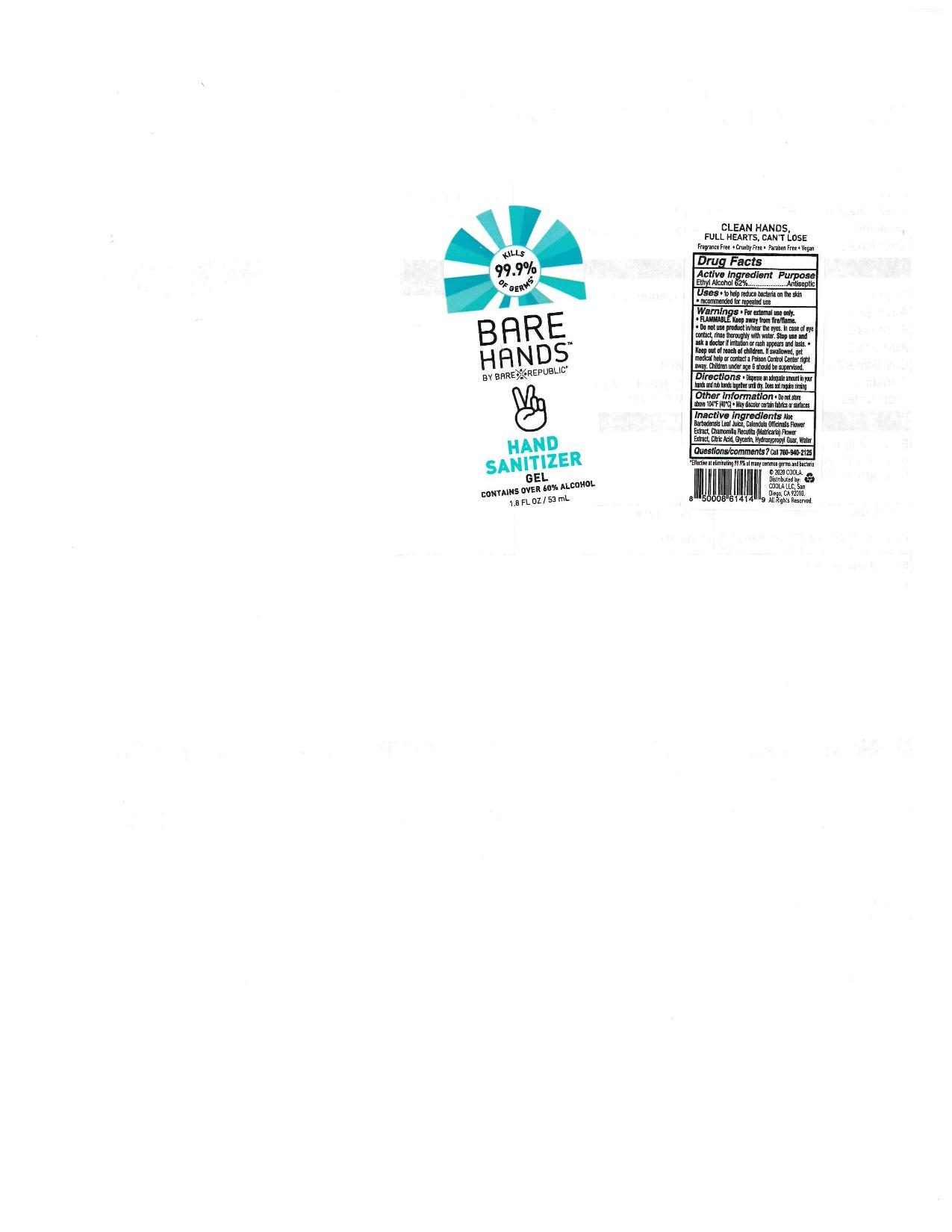 DRUG LABEL: Bare Hands
NDC: 76150-240 | Form: GEL
Manufacturer: Bell International Laboratories, Inc.
Category: otc | Type: HUMAN OTC DRUG LABEL
Date: 20200518

ACTIVE INGREDIENTS: ALCOHOL 62 mL/100 mL
INACTIVE INGREDIENTS: CALENDULA OFFICINALIS FLOWER; CHAMOMILE; WATER; GUARAPROLOSE (1300 MPA.S AT 1%); GLYCERIN; ALOE VERA LEAF; CITRIC ACID MONOHYDRATE

Coola Bare Hands Hand Sanitizer Gel

Active Ingredient

Ethyl Alcohol 62%

Purpose

Antiseptic

Uses

to help reduce bacteria on the skin

recommended for repeated use

Warnings

For external use only

Flammable. Keep away from fire/flame.

Do not use product in/near the eyes. In case of eye contact, rinse thoroughly with water.

Stop use and ask a doctor if irritation or rash appears and lasts.

Keep out of reach of children. If swallowed, get medical help or contact a Poison Control Center right away. Children under age 6 should be supervised.

Directions

Dispense an adequate amount in your hands and rub hands together until dry. Does not require rinsing.

Other Information

do not store above 104 F (40 C). May discolor certain fabrics or surfaces

Inactive Ingredients

Aloe Barbadensis Leaf Juice, Calendula Officinalis Flower Extract, Chamomilla Recutita (Matricaria) Flower Extract, Citric Acid, Glycerin, Hydroxypropyl Guar, Water